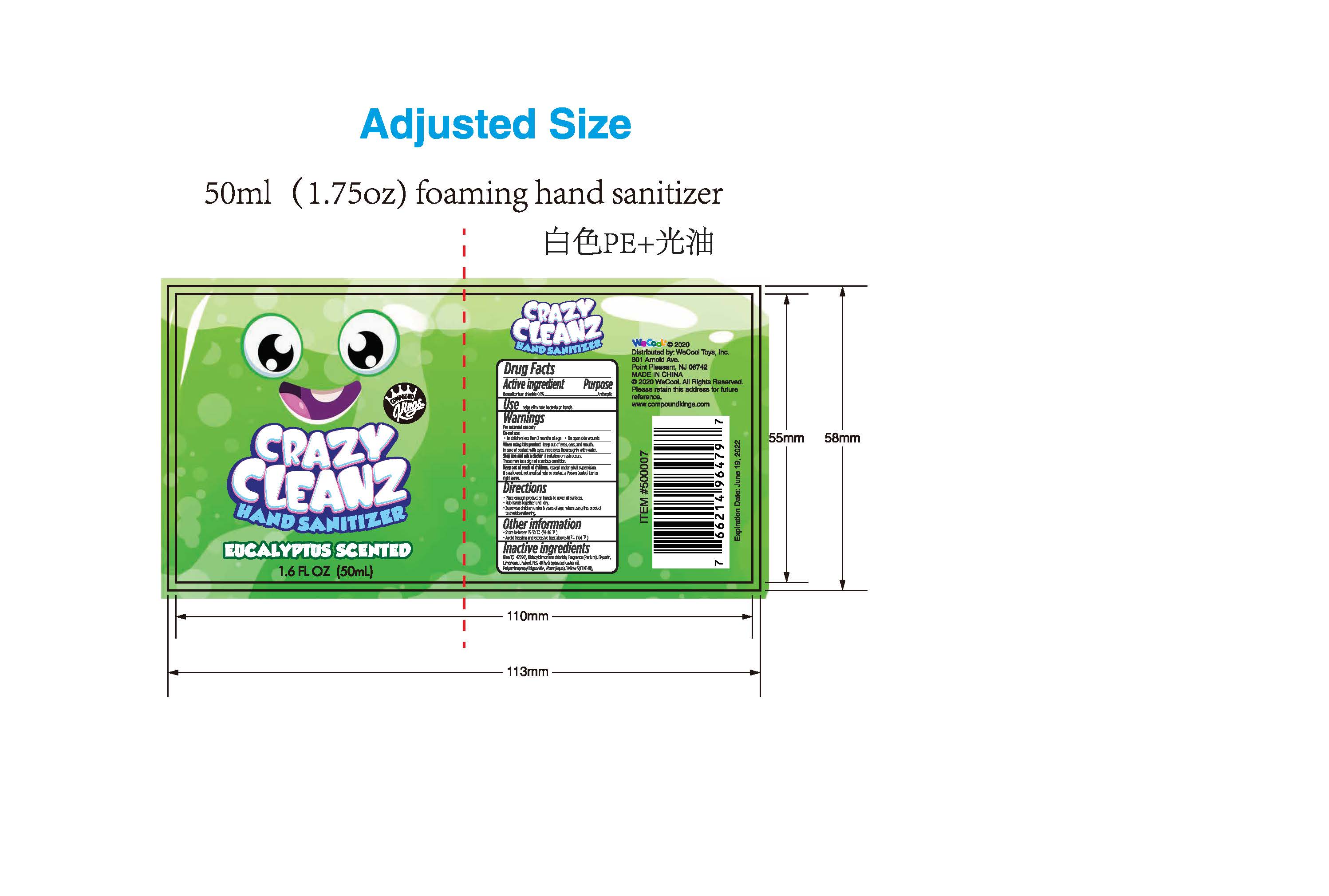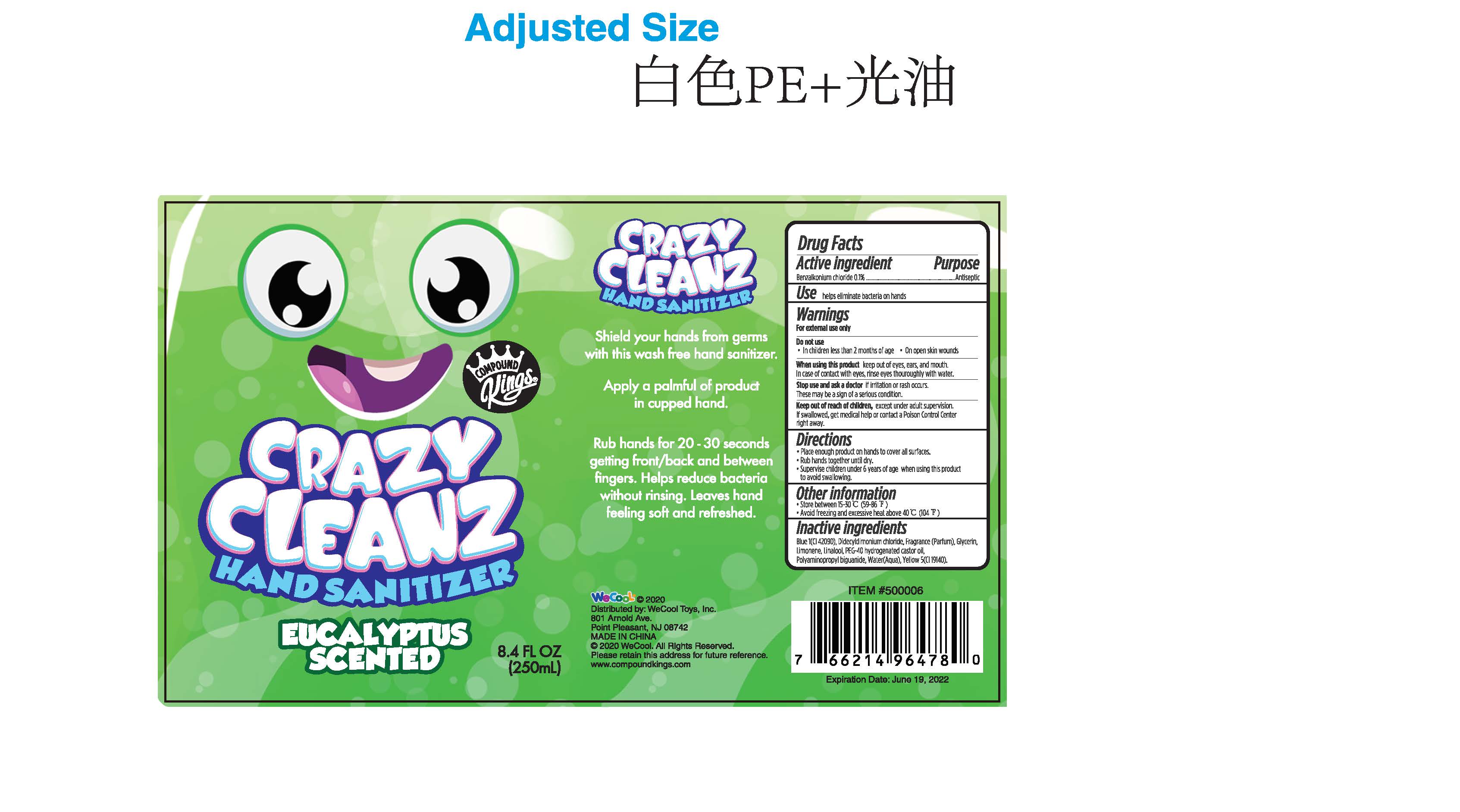 DRUG LABEL: Crazy Cleanz Hand Sanitizer Eucalyptus Scented
NDC: 51706-919 | Form: GEL
Manufacturer: Landy International
Category: otc | Type: HUMAN OTC DRUG LABEL
Date: 20220321

ACTIVE INGREDIENTS: BENZALKONIUM CHLORIDE 0.1 g/100 g
INACTIVE INGREDIENTS: FD&C BLUE NO. 1; DIDECYLDIMONIUM CHLORIDE; LIMONENE, (+)-; LINALOOL, (+/-)-; GLYCERIN; WATER; POLYAMINOPROPYL BIGUANIDE; FD&C YELLOW NO. 5; POLYOXYL 40 HYDROGENATED CASTOR OIL

51706-919 Crazy Cleanz Hand Sanitizer Eucalyptus Scented Benzalkonium chloride(0.1%)

Active Ingredient(s)

Benzalkonium Chloride 0.1%

Purpose

Antiseptic

Use

helps eliminate bacteria on hands

Warnings

For external use only.
Do not use
In children less than 2 months of age. on open skin wounds
When using this product keep out of eyes, ear, and mouth.
In case of contact with eve, rinse eyes thouroughly with water
Stop use and ask a doctor if irritation or rash occurs,
These may be a sign of a serious condition.

Keep out of reach of children. except under adult supervision.

If swallowed, get medical help or contact a poison control center right away.

Directions

Place enough product on hands to cover all surfaces.
Rub hands together until dry.
Supervise children under 6 years of age When using this product
to avoid swallowing.

Inactive ingredients

Blue 1(I 42090), Didecyldimonium chloride, Fragrance (Parfum), Glycerin,
Limonene, Linalool, PEG-40 hydrogenated castor oil,
Polyaminopropyl biguanide, Water(Aqua), Yellow 5(CI 19140),